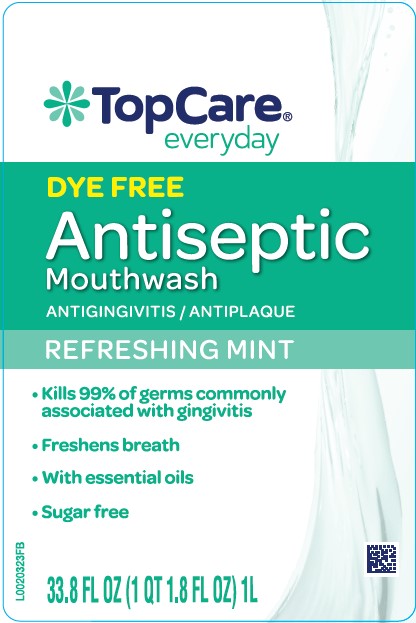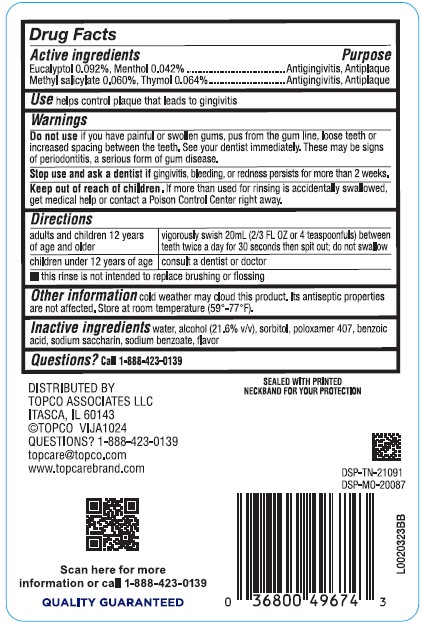 DRUG LABEL: Antispetic
NDC: 76162-567 | Form: MOUTHWASH
Manufacturer: Topco Associates LLC
Category: otc | Type: HUMAN OTC DRUG LABEL
Date: 20260213

ACTIVE INGREDIENTS: EUCALYPTOL 0.92 mg/1 mL; MENTHOL 0.42 mg/1 mL; METHYL SALICYLATE 0.6 mg/1 mL; THYMOL 0.64 mg/1 mL
INACTIVE INGREDIENTS: ALCOHOL; SORBITOL; POLOXAMER 407; BENZOIC ACID; SACCHARIN SODIUM; SODIUM BENZOATE; WATER

Top Care 567.000/567AA
Dye-Free Antiseptic Mint Mouthrinse

Active ingredients

Eucalyptol 0.092%

Menthol 0.042%

Methyl salicylate 0.060%

Thymol 0.064%

Purpose

Antigingivitis, Antiplaque

Use

helps control plaque that leads to gingivitis

Warnings

for this product

Do not use

if you have painful or swollen gums, pus from the gum line, loose teeth or increased spacing between the teeth. See your dentist immediately. These may be signs of periodontitis, a serious form of gum disease.

Stop use and ask a dentist if

gingivitis, bleeding, or redness persists for more than 2 weeks.

Keep out of reach of children.

If more than used for rinsing is accidentally swallowed, get medical help or contact a Poison Control Center right away.

Directions

adults and children 12 years of age and older - vigorously swish 20 mL (2/3 FL OZ or 4 teaspoonfuls) between teeth twice a day for 30 seconds then spit out; do not swallow

children under 12 years of age - consult a dentist or doctor

- this rinse is not intended to replace brushing or flossing

Other information

cold weather may cloud this product. Its antiseptic properties are not affected. Store at room temperature (59°-77°F).

Inactive ingredients

water, alcohol 21.6%, sorbitol, poloxamer 407, benzoic acid, sodium saccharin, sodium benzoate, flavor

Questions?

Call 1-888-423-0139

Tamper Evident Statement

SEALED WITH PRINTED NECKBAND FOR YOUR PROTECTION

ADVERSE REACTION

DISTRIBUTED BY

TOPCO ASSOCIATES, LLC

ITASCA, IL 60143

©TOPCO VIJA1024

QUESTIONS? 1-888-423-0139

topcare@topco.com

www.topcarebrand.com

Scan here for more information or call 1-888-423-0139

DSP-TN-21091

DSP-MO-20087

Principal display panel

TopCare®

everyday

DYE FREE

Antiseptic

Mouthwash

ANTIGINGIVITIS/ANTIPLAQUE

REFRESHING MINT

- Kills 99% of germs commonly associated with gingivitis
- Freshens breath
- With essential oils
- Sugar free

33.8 FL OZ (1QT 1.8 FL OZ) 1 L